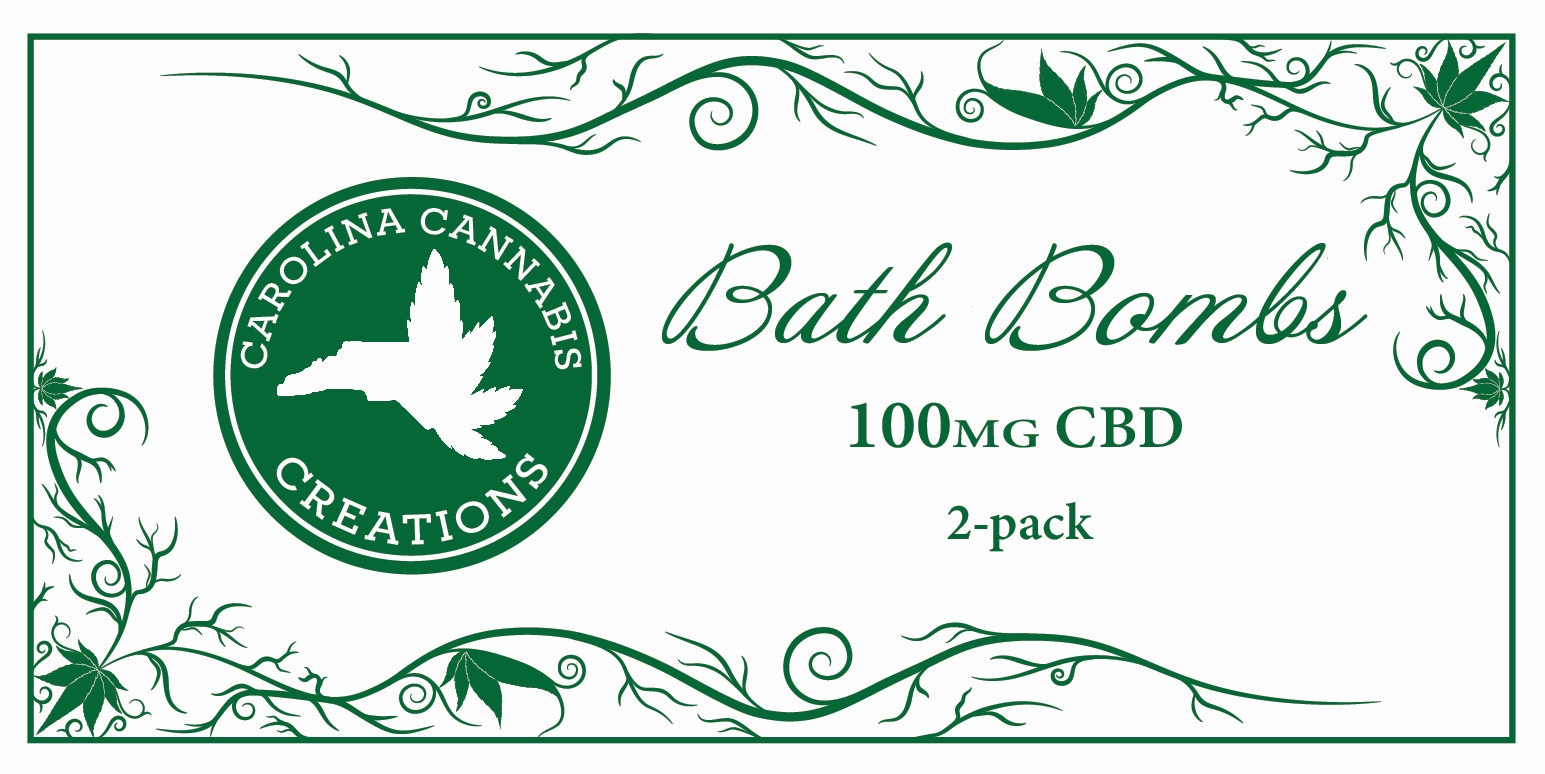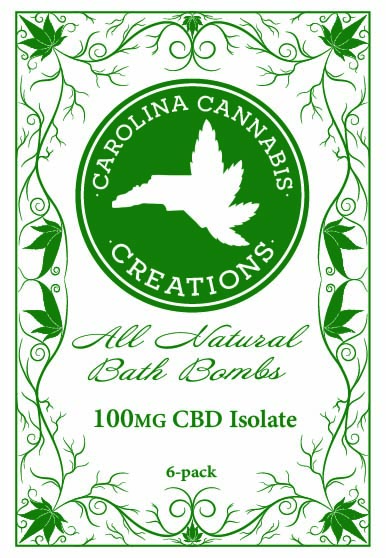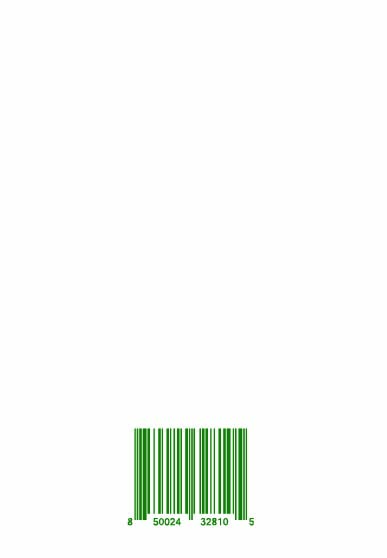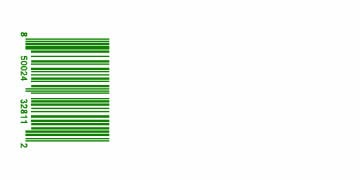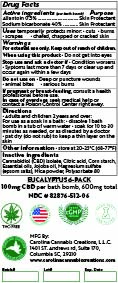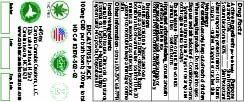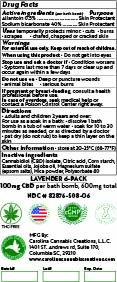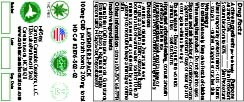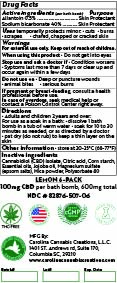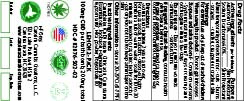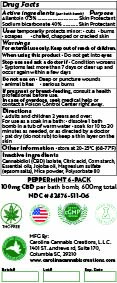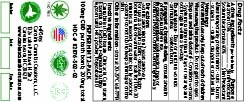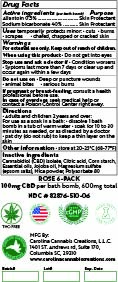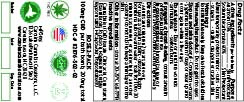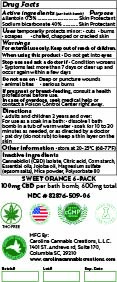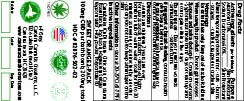 DRUG LABEL: Bath Bomb 2-pack (Rose)
NDC: 82876-504 | Form: TABLET, SOLUBLE
Manufacturer: Carolina Cannabis Creations LLC
Category: otc | Type: HUMAN OTC DRUG LABEL
Date: 20250806

ACTIVE INGREDIENTS: ALLANTOIN 1.1 g/186.16 g; SODIUM BICARBONATE 82 g/186.16 g
INACTIVE INGREDIENTS: POLYSORBATE 80 1.9 g/186.16 g; STARCH, CORN 18.7 g/186.16 g; ANHYDROUS CITRIC ACID 38 g/186.16 g; MICA 0.7 g/186.16 g; JOJOBA OIL 2.7 g/186.16 g; CANNABIDIOL 0.21 g/186.16 g; ROSE OIL 3.25 g/186.16 g; MAGNESIUM SULFATE ANHYDROUS 37.6 g/186.16 g

Bath bomb (Allantoin & Sodium bicarbonate)

Active Ingredients

Allantoin 0.5%

Sodium Bicarbonate 40%

Purpose

Skin Protectant

Skin Protectant

uses

Temporarily protects minor cuts, burns, scrapes, chafed, chapped, or cracked skin.

Warnings

For external use only.

Keep out of reach of children

When using this product

Do not get into eyes

Stop use and ask a doctor if

The condition worsens, symptoms last more than 7 days or clear up and occur again within a few days

Stop use and ask a doctor if

Condition worsens, symptoms last more than 7 days or clears up and occurs again within a few days

Do not use on

Deep or puncture wounds, animal bites, serious burns.

if pregnant or breast feeding

consult a health professional before use.

in case of overdose

seek medical help or contact a poison control center right away.

Directions

Adults and children 2 years and over. For use as soak in bath, dissolve 1 bath bomb in warm tub of water, Soak for 10 to 30 minutes as needed, or as directed by doctor. Pat dry (do not rub) to leave a thin layer on the skin

other information

store at 20-25C (68-77 F)

Inactive ingredients

Cannabidiol (CBD) Isolate, Citric acid, Corn Starch, essential oils, Jojoba oil, Magnesium Sulfate (Epsom salts), Mica powder, polysorbate 80.